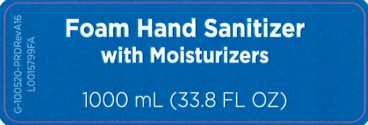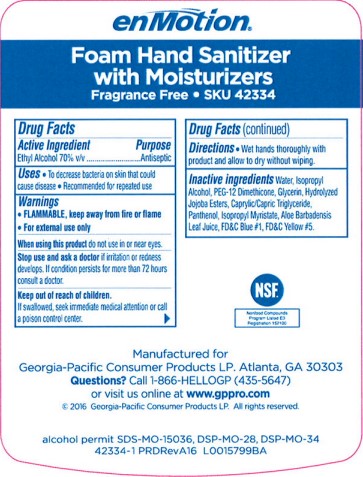 DRUG LABEL: enMotion Foam


NDC: 54622-708 | Form: SOLUTION
Manufacturer: Georgia-Pacific Consumer Products LP
Category: otc | Type: HUMAN OTC DRUG LABEL
Date: 20260204

ACTIVE INGREDIENTS: ALCOHOL 70 mg/1 mL
INACTIVE INGREDIENTS: ISOPROPYL ALCOHOL; WATER; PEG-12 DIMETHICONE; GLYCERIN; HYDROLYZED JOJOBA ESTERS (ACID FORM); GLYCERYL CAPRYLATE/CAPRATE; PANTHENOL; ISOPROPYL MYRISTATE; ALOE VERA LEAF; FD&C BLUE NO. 1; FD&C YELLOW NO. 5

enMotion 708.000/708AA
Foam hand sanitizer with moisturizers

Claims

enMotion®

Foam Hand Sanitizer

with Moisturizers

Fragrance Free • SKU 42334

Active ingredient

Ethyl Alcohol 70% v/v

Purpose

Antiseptic

Uses

- To decrease bacteria on skin that could cause disease
- Recommended for repeated use

Warnings

- FLAMMABLE, keep away from fire or flame
- For external use only

When using this product

do not use in or near eyes.

Stop use and ask a doctor

if irritation or redness develops. If condition persists for more than 72 hours consult a doctor.

Keep out of reach of children.

If swallowed, seek immediate medical attention or call a poison control center.

Directions

Wet hands thoroughly with product and allow to dry without wiping.

Inactive ingredients

Water, Isopropyl Alcohol, PEG-12 Dimethicone, Glycerin, Hydrolyzed Jojoba Esters, Caprylic/Capric Triglyceride, Panthenol, Isopropyl Myristate, Aloe Barbadensis Leaf Juice, FD&C Blue #1, FD&C Yellow #5.

ADVERSE REACTION

Manufactured for Georgia-Pacific Consumer Products LP. Atlanta, GA 30303

Questions? Call 1-866-HELLOGP (435-5647)

or visit us online at www.gppro.com

©2016 Georgia Pacific Consumer Products LP. All rights reserved.

alcohol permit SDS-MO-15036, DSP-MO-28, DSP-MO-34

42334-1 PRDRevA16

principal display panel

Foam Hand Sanitizer with Moisturizers

G-100520-PRDRevA16

1000 mL (33.8 FL OZ)